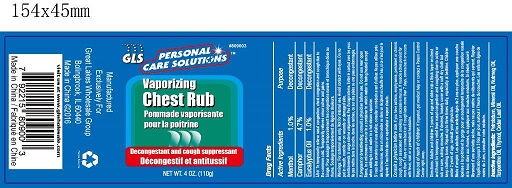 DRUG LABEL: nasal decongestant
NDC: 64092-403 | Form: GEL
Manufacturer: Great Lakes Wholesale, Marketing, and Sales, INC
Category: otc | Type: HUMAN OTC DRUG LABEL
Date: 20160805

ACTIVE INGREDIENTS: CAMPHOR (SYNTHETIC) 5.17 1/110 g; EUCALYPTUS OIL 1.1 1/110 g; MENTHOL 1.1 1/110 g
INACTIVE INGREDIENTS: PETROLATUM

DESCRIPTION

GLS PERSONAL CARE SOLUTIONS

Vaporizing Chest Rub

Decongestant and cough suppressant

NET WT. 4 OZ. (110g)

Active Ingredients Purpose

Menthol 1.0%........................................................................Decongestant

Camphor 4.7%......................................................................Decongestant

Eucalytus Oil 1.0%................................................................Decongentant

PURPOSE

Temporarily relieve nasal congestion, chest congestion and cough.

INDICATIONS AND USAGE

To temporarily relieve nasal congestion, chest congestion and cough due to the common cold.

Temporarily relieves minor aches and pains.

WARNINGS

For external use only.

Not for internal use.

Avoid contact with eyes.

Do not put in mouth, notsrils or on wounds or damaged skin.

Do not use near open flame, in a microwave oven or in a container in which water is being heated, except when adding to cold water in a hot steam vaporizer.

PREGNANCY OR BREAST FEEDING

Consult a physician before use.

ASK DOCTOR

If you have asthma, emphysema, persistent or chronic cough, cough associated with smoking or excessive mucus.

If muscle aches persist for more than 7 days or come back, or if cough lasts more than 7 days, comes back or occurs with fever, rash or a persistent headache.

KEEP OUT OF REACH OF CHILDREN

if ingested, get medical help or contact a Poison Control Center right away.

INSTRUCTIONS FOR USE

Adults and children 2 years of age and older, rub a thick layer on chest and throat for temporary relief from nasal congestion and coughing due to colds or rub on sore, aching muscles.

If desired, loosely cover with a soft dry cloth, but keep clothing loose.

Repeat up to three times daily, especially at bedtime.

Children under 2 years of age, consult your physician.

DOSAGE AND ADMINISTRATION

Topical decongestant and cough suppressant gel

1.0% Menthol

4.7% Camphor

1.0% Eucalyptus Oil

INACTIVE INGREDIENT

Petrolatum, Mineral oil, Nutmeg oil, Turpentine Oil, Thymol, Cedar Leaf Oil.